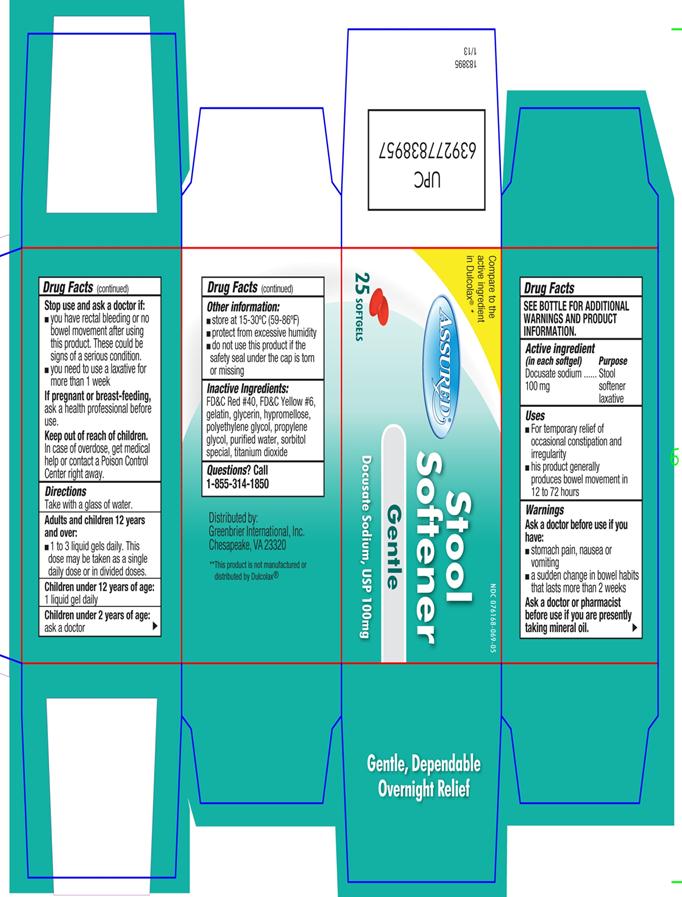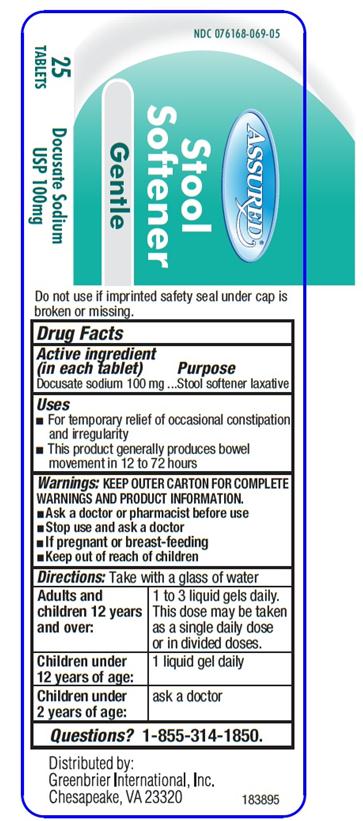 DRUG LABEL: Stool Softener
NDC: 76168-069 | Form: CAPSULE, LIQUID FILLED
Manufacturer: Velocity Pharma
Category: otc | Type: HUMAN OTC DRUG LABEL
Date: 20130511

ACTIVE INGREDIENTS: DOCUSATE SODIUM 100 mg/1 1
INACTIVE INGREDIENTS: FD&C RED NO. 40; FD&C YELLOW NO. 6; GELATIN; HYPROMELLOSES; PROPYLENE GLYCOL; SORBITOL; TITANIUM DIOXIDE; WATER; GLYCERIN

Docusate Sodium, USP 100mg

Active Ingredient

(in each softgel)

Docusate Sodium 100 mg

Purpose

Stool softener laxative

Uses

- for temporary relief of occasional constipation and irregularity
- this product generally produces bowel movement in 12 to 72 hours

Warnings

Ask a doctor before use if you have:

- stomach pain, nausea or vomiting
- a sudden change in bowel habits that lasts more than 2 weeks

Ask a doctor or pharmacist before use if you are presently taking mineral oil.

Stop use and ask a doctor if:

- you have rectal bleeding or no bowel movement after using this product. This could be signs of a serious condition.
- you need to use laxative for more than 1 week.

If pregnant or breast-feeding, ask a health professional before use.

Keep out of reach of children.

In case of overdose, get medical help or contact a Poison Control Center right away.

Directions

Take with glass of water

adults and children 12 years and over:

- 1 to 3 liquid gels daily. This dose may be taken as single daily dose or in divided doses.
  Children under 12 years of age:
- 1 liquid gel daily

Children under 2 years of age

Ask a doctor

Other Information

- store at 15-30 °C (59-86 °F)
- protect from excessive humidity
- do not use this product if the safety seal under the cap is torn or missing

Inactive Ingredients

FD&C Red #40, FD&C Yellow #6, gelatin, glycerin, hypromellose, polyethylene glycol, propylene glycol, purified water, sorbitol special, titanium dioxide

Questions or Comments

Call 1-855-314-1850

PACKAGE LABEL.PRINCIPAL DISPLAY PANEL

NDC: 076168-069-05 – 25 COUNT